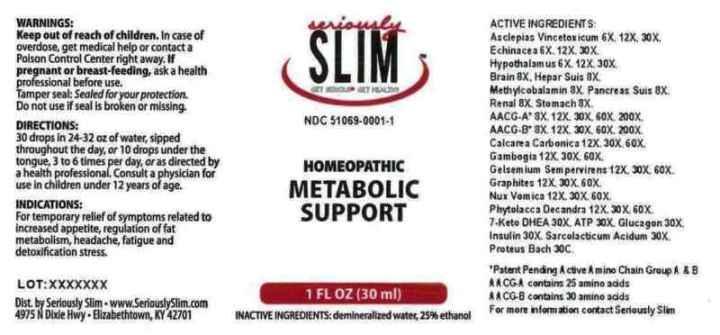 DRUG LABEL: Metabolic Support
NDC: 51069-0001 | Form: LIQUID
Manufacturer: Seriously Slim
Category: homeopathic | Type: HUMAN OTC DRUG LABEL
Date: 20120906

ACTIVE INGREDIENTS: CYNANCHUM VINCETOXICUM ROOT 6 [hp_X]/1 mL; ECHINACEA, UNSPECIFIED 6 [hp_X]/1 mL; SUS SCROFA HYPOTHALAMUS 6 [hp_X]/1 mL; PORK BRAIN 8 [hp_X]/1 mL; PORK LIVER 8 [hp_X]/1 mL; METHYLCOBALAMIN 8 [hp_X]/1 mL; SUS SCROFA PANCREAS 8 [hp_X]/1 mL; PORK KIDNEY 8 [hp_X]/1 mL; SUS SCROFA STOMACH 8 [hp_X]/1 mL; APC-356433 8 [hp_X]/1 mL; APC-356434 8 [hp_X]/1 mL; OYSTER SHELL CALCIUM CARBONATE, CRUDE 12 [hp_X]/1 mL; GAMBOGE 12 [hp_X]/1 mL; GELSEMIUM SEMPERVIRENS ROOT 12 [hp_X]/1 mL; GRAPHITE 12 [hp_X]/1 mL; STRYCHNOS NUX-VOMICA SEED 12 [hp_X]/1 mL; PHYTOLACCA AMERICANA ROOT 12 [hp_X]/1 mL; 7-OXO-PRASTERONE 30 [hp_X]/1 mL; ADENOSINE TRIPHOSPHATE 30 [hp_X]/1 mL; GLUCAGON 30 [hp_X]/1 mL; INSULIN PORK 30 [hp_X]/1 mL; LACTIC ACID, L- 30 [hp_X]/1 mL; PROTEUS INCONSTANS 30 [hp_C]/1 mL
INACTIVE INGREDIENTS: WATER; ALCOHOL

Metabolic Support

Active Ingredients

ACTIVE INGREDIENTS: Asclepias vincetoxicum 6X, 12X, 30X, Echinacea 6X, 12X, 30X, Hypothalamus (suis) 6X, 12X, 30X, Brain (suis) 8X, Hepar suis 8X, Methylcobalamin 8X, Pancreas suis 8X, Renal (suis) 8X, Stomach (suis) 8X, AACG-A 8X, 12X, 30X, 60X, 200X, AACG-B 8X, 12X, 30X, 60X, 200X, Calcarea carbonica 12X, 30X, 60X, Gambogia 12X, 30X. 60X, Gelsemium sempervirens 12X, 30X, 60X, Graphites 12X, 30X, 60X, Nux vomica 12X, 30X, 60X, Phytolacca decandra 12X, 30X, 60X, 7-keto DHEA 30X, ATP 30X, Glucagon 30X, Insulin 30X, Sarcolacticum acidum 30X, Proteus bach 30C.

Purpose

INDICATIONS: For temporary relief of symptoms related to increased appetite, regulation of fat metabolism, headache, fatigue and detoxification stress.

Warnings

WARNINGS: Keep out of reach of children. In case of overdose, get medical help or contact a Poison Control Center right away.

If pregnant or breast-feeding, ask a health professional before use.

Tamper seal: Sealed for your protection. Do not use if seal is broken.

Dosage

DIRECTIONS: 30 drops in 24-32 oz of water, sipped throughout the day, or 10 drops under the tongue, 3 to 6 times per day, or as directed by a health professional. Consult a physician for use in children under 12 years of age.

Inactive Ingredients

INACTIVE INGREDIENTS: Demineralized water, 25% ethanol.

KEEP OUT OF REACH OF CHILDREN. In case of overdose, get medical help or contact a Poison Control Center right away

Indications

INDICATIONS: For temporary relief of symptoms related to increased appetite, regulation of fat metabolism, headache, fatigue and detoxification stress.

Questions

Dist by Seriously Slim

4975 N Dixie Hwy

Elizabethtown, KY 42701

www.SeriouslySlim.com

Package Label

seriously SLIM

NDC 51069-0001-1

HOMEOPATHIC

METABOLIC SUPPORT

1 FL OZ (30 ml)